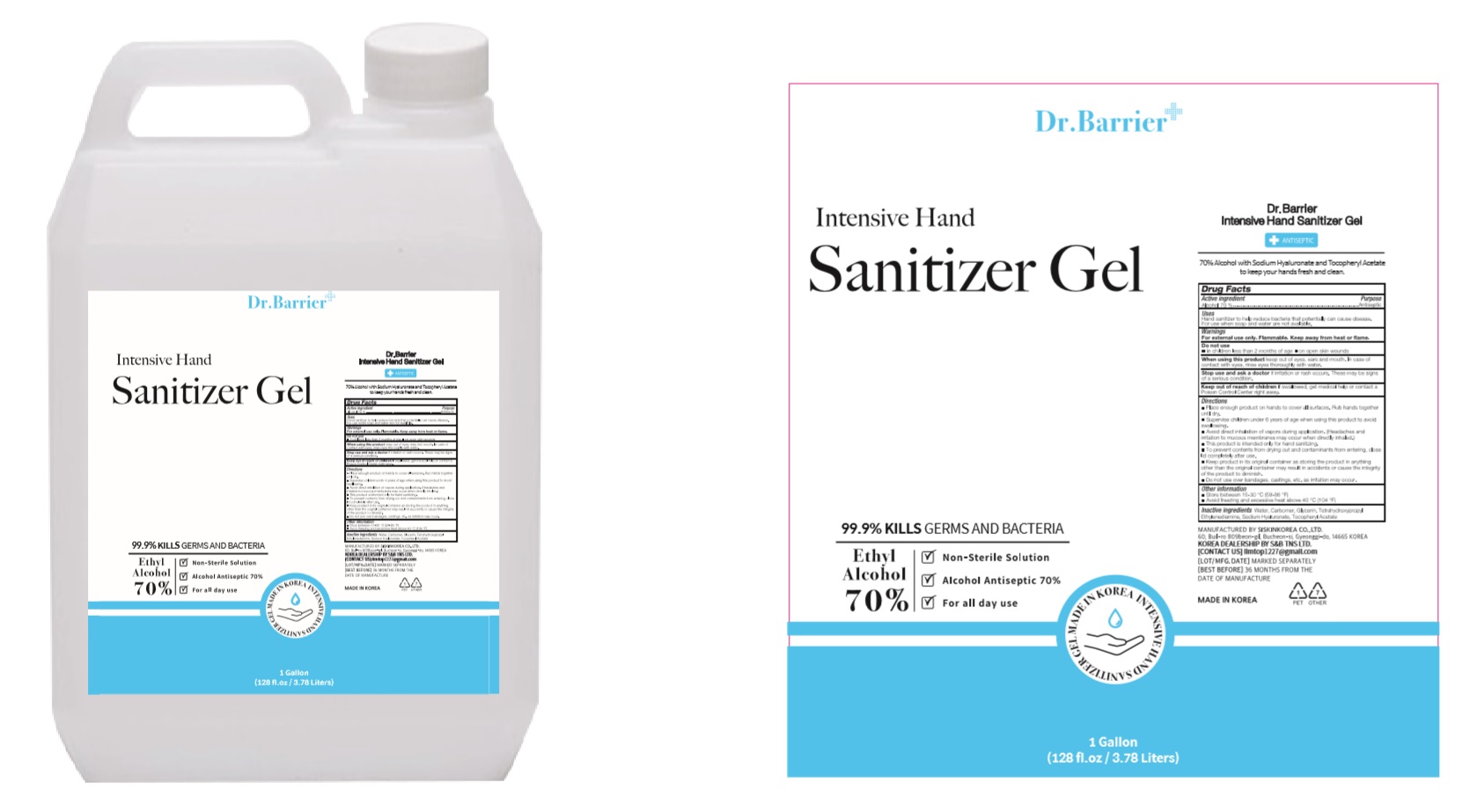 DRUG LABEL: Dr. Barrier Intensive Hand Sanitizer Gel
NDC: 74514-0801 | Form: GEL
Manufacturer: SISKINKOREA CO.,LTD.
Category: otc | Type: HUMAN OTC DRUG LABEL
Date: 20200812

ACTIVE INGREDIENTS: ALCOHOL 2649.5 mL/3785 mL
INACTIVE INGREDIENTS: GLYCERIN; .ALPHA.-TOCOPHEROL ACETATE; EDETOL; WATER; HYALURONATE SODIUM; CARBOMER HOMOPOLYMER, UNSPECIFIED TYPE

Dr. Barrier Intensive Hand Sanitizer Gel | 3785 mL | 74514-0801-1